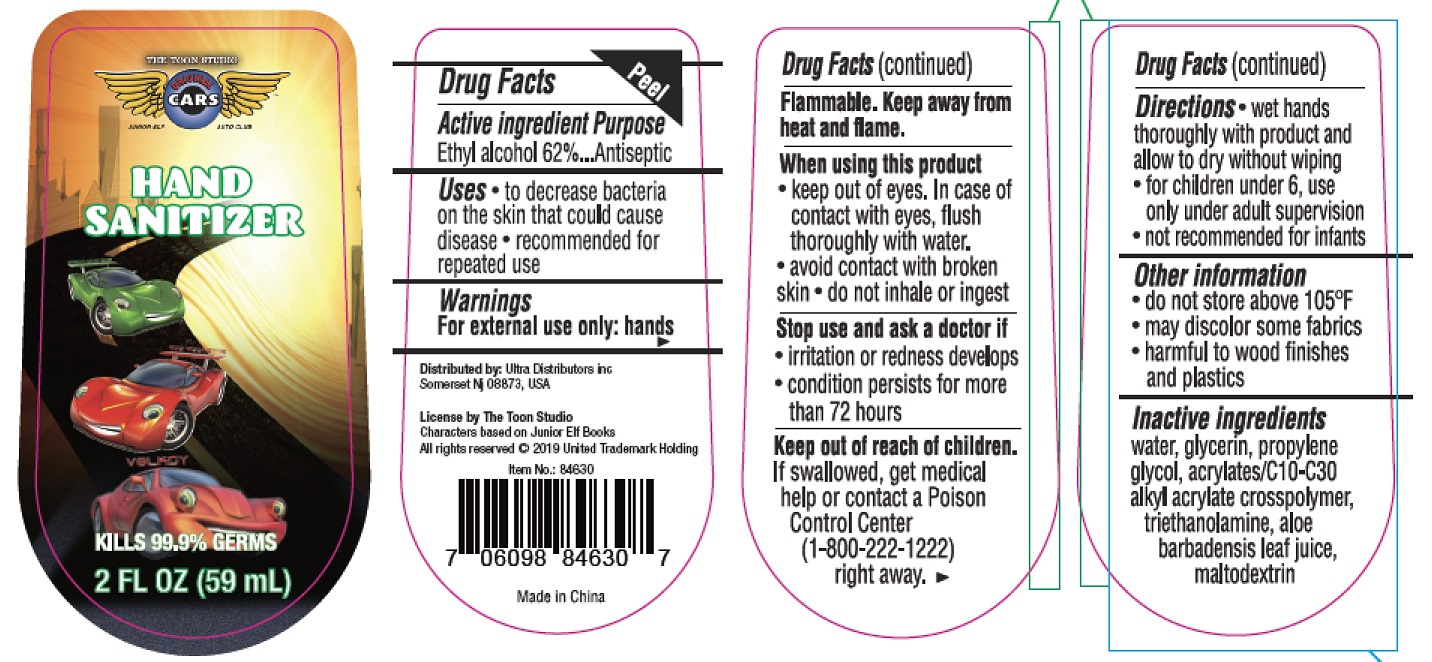 DRUG LABEL: HAND SANITIZER
NDC: 78495-002 | Form: GEL
Manufacturer: Ultra Distributors Inc
Category: otc | Type: HUMAN OTC DRUG LABEL
Date: 20200904

ACTIVE INGREDIENTS: ALCOHOL 62 mL/100 mL
INACTIVE INGREDIENTS: MALTODEXTRIN; CARBOMER COPOLYMER TYPE A (ALLYL PENTAERYTHRITOL CROSSLINKED); ALOE VERA LEAF; TROLAMINE; WATER; GLYCERIN; PROPYLENE GLYCOL

HAND SANITIZER Cars

Active ingredient

Ethyl Alcohol 62%

Purpose

Antiseptic

Uses

- to decrease bacteria on the skin that could cause disease
- recommended for repeated use

Warnings

For external use only: hands

Flammable. Keep away from fire or flame

When using this product

- keep out of eyes. In case of contact with eyes, flush thoroughly with water.
- avoid contact with broken skin.
- do not inhale or ingest.

Stop use and ask a doctor if

- irritation or redness develops.
- condition persists for more than 72 hours

Keep out of reach of children. If swallowed, get medical help or contact a poison control center(1-800-222-1222)right away.

Directions

- wet hands thoroughly with product and allow to dry without wiping.
- for children under 6 , use only under adult supervision.
- not recommended for infants .

Other information

- do not store above 105°F
- may discolor some fabics
- harmful to wood finished and plastics

Inactive ingredients

water, glycerin, propylene glycol, acrylates/C10-C30 alkyl acrylate crosspolymer, triethanolamine, aloe barbadensis leaf juice, maltodextrin